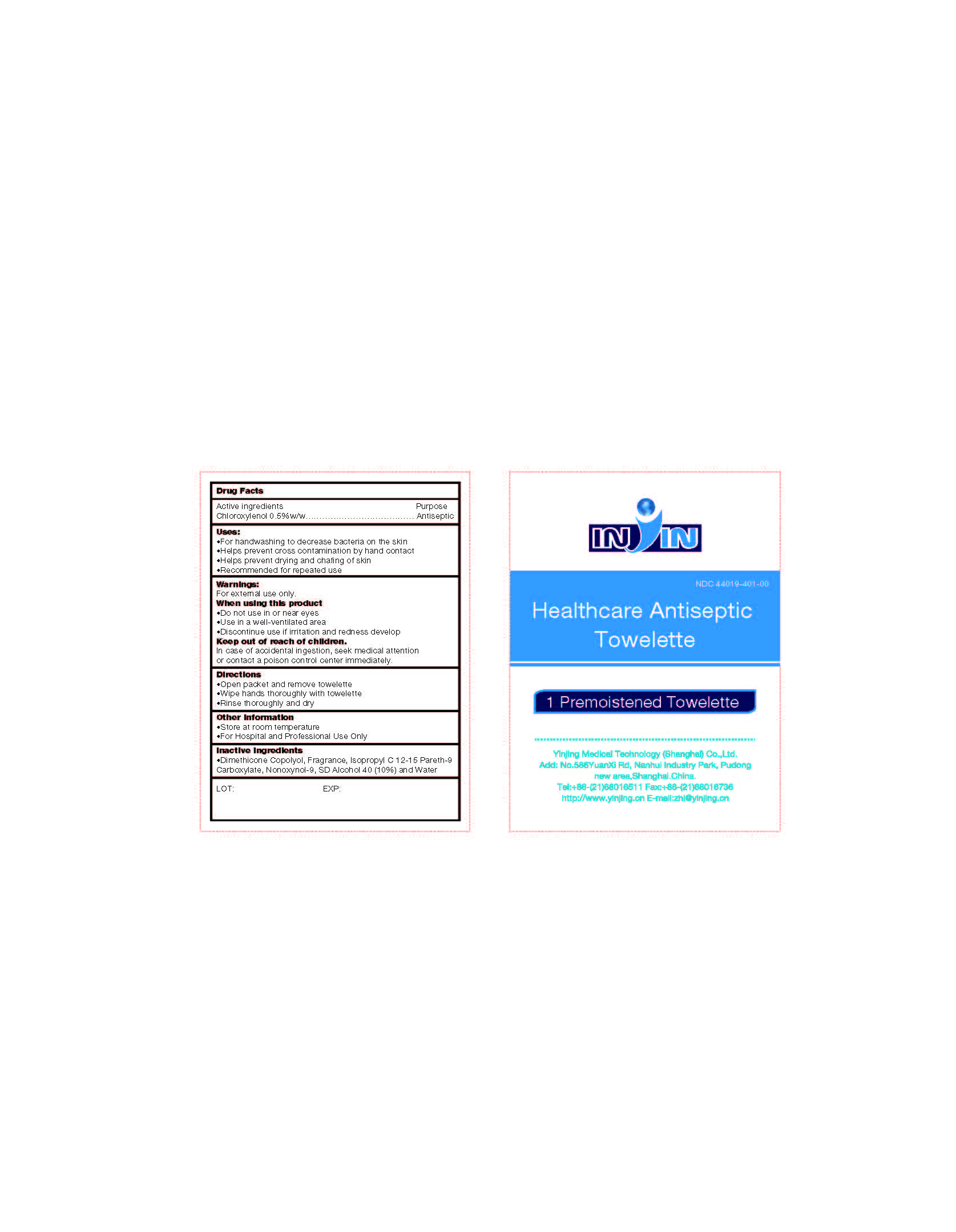 DRUG LABEL: Healthcare Antiseptic Towelette
NDC: 44019-401 | Form: LIQUID
Manufacturer: Yinjing Medical Technology (Shanghai) Co., Ltd.
Category: otc | Type: HUMAN OTC DRUG LABEL
Date: 20171227

ACTIVE INGREDIENTS: CHLOROXYLENOL 0.5 g/100 g
INACTIVE INGREDIENTS: DIMETHICONE; ISOPROPYL ALCOHOL; C12-15 PARETH-9; NONOXYNOL-9; ALCOHOL; WATER

Healthcare Antiseptic Towelette

ACTIVE INGREDIENT

Chloroxylenol 0.5%

PURPOSE

Antiseptic

Uses:

- For handwashing to decrease bacteria on the skin
- Helps prevent cross contamination by hand contact
- Helps prevent drying and chafing of skin
- Recommended for repeated use

Warnings:

For external use only.

When using this product

- Do not use in or near eyes
- Use in a well-ventilated area
- Discontinue use if irritation and redness develop

Keep out of reach of children.

In case of accidental ingestion, seek medical attention or contact a poison control center immediately.

Directions

- Open packet and remove towelette
- Wipe hands thoroughly with towelette
- Rinse thoroughly and dry

Other Information

- Store at room temperature
- For Hospital and Professional Use Only

Inactive Ingredients

- Dimethicone Copolyol, Fragrance, Isopropyl C 12-15 Pareth-9 Carboxylate, Nonoxynol-9, SD Alcohol 40 (10%) and Water